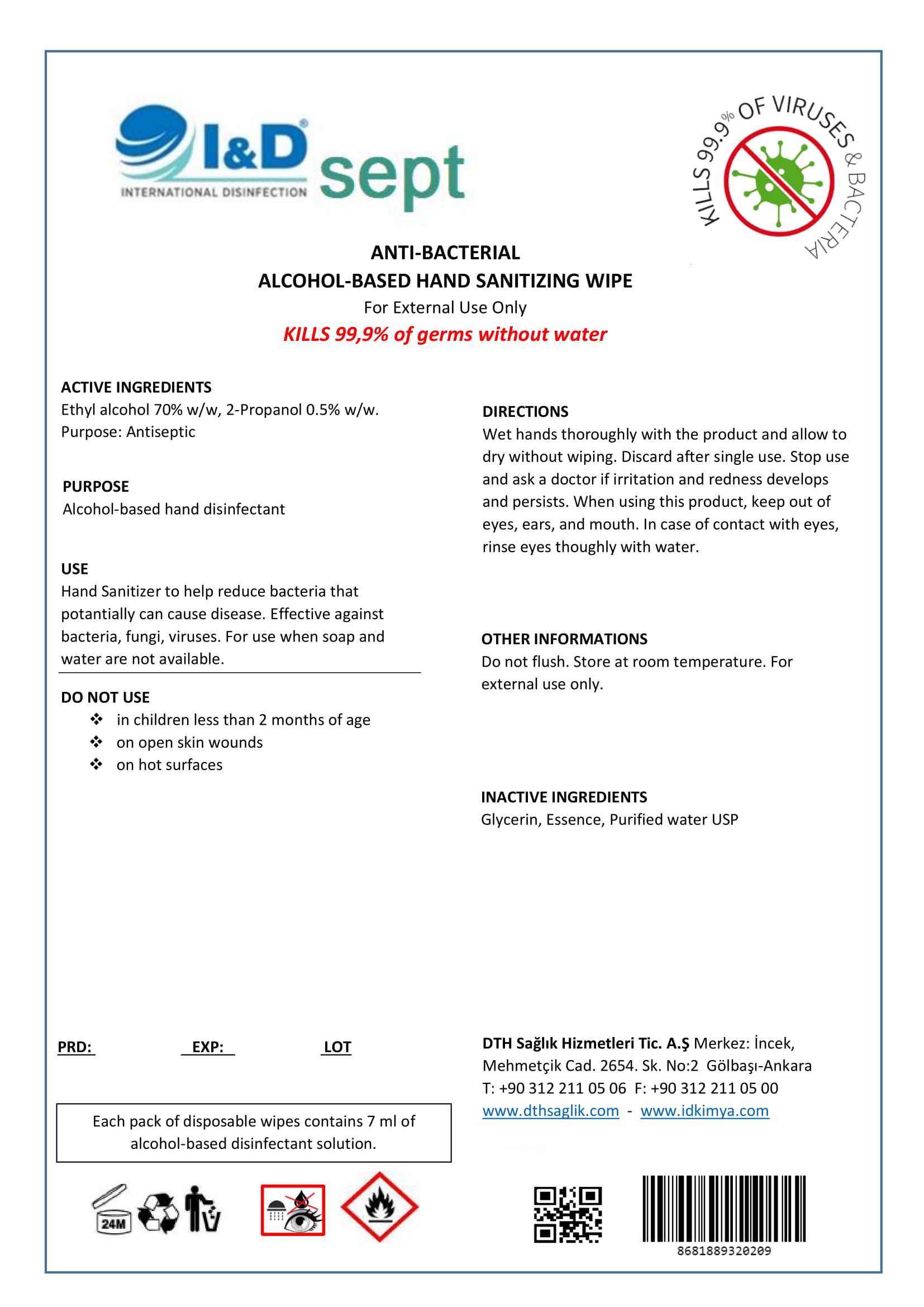 DRUG LABEL: I D SEPT ANTI BACTERIAL ALCOHOL BASED HAND SANITIZING WIPE
NDC: 78992-609 | Form: CLOTH
Manufacturer: DTH SAGLIK HIZMETLERI TICARET ANONIM SIRKETI
Category: otc | Type: HUMAN OTC DRUG LABEL
Date: 20200629

ACTIVE INGREDIENTS: ISOPROPYL ALCOHOL 0.5 mL/100 mL; ALCOHOL 70 mL/100 mL
INACTIVE INGREDIENTS: GLYCERIN; WATER

Hand Sanitizer Wipe

Active Ingredient(s)

Ethyl alcohol 70% w/w, 2-Propanol 0.5% w/w

Purpose

Antiseptic

Alcohol-based hand disinfectant

Use

Hand Sanitizer to help reduce bacteria that potentially can cause disease. For use when soap and water are not available.

Warnings

For external use only.

Do not use

- in children less than 2 months of age
- on open skin wounds
- on hot surfaces

When using this product, keep out of eyes, ears, and mouth. In case of contact with eyes, rinse eyes thoroughly with water.

Discard after single use. Do not flush.

Stop use and ask a doctor if irritation and redness develops and persists.

Directions

Wet hands thoroughly with the product and allow to dry without wiping.

Other information

Store at room temperature.

Inactive ingredients

Glycerin, Fragrance, Citric acid, Purified water USP

Keep out of reach of children.

Package Label - Principal Display Panel

DTH Saglik Hizmetleri Tic. A.S. Merkez: Incek Mehmetcik Cad. 2654. Sk. No:2 Golbasi-Ankara

T: +90 312 211 05 06 F: +90 312 211 05 00

wwww.dthsaglik.com - www.idkimya.com

I& D sept INTERNATIONAL DISINFECTION

ANTI-BACTERIAL ALCOHOL BASED HAND SANITIZING WIPE

For External Use Only

KILLS 99,9% of germs without water

KILLS 99,9% VIRUSES & BACTERIA

Each pack of disposable wipes contains 7 ml of alcohol-based disinfectant solution.